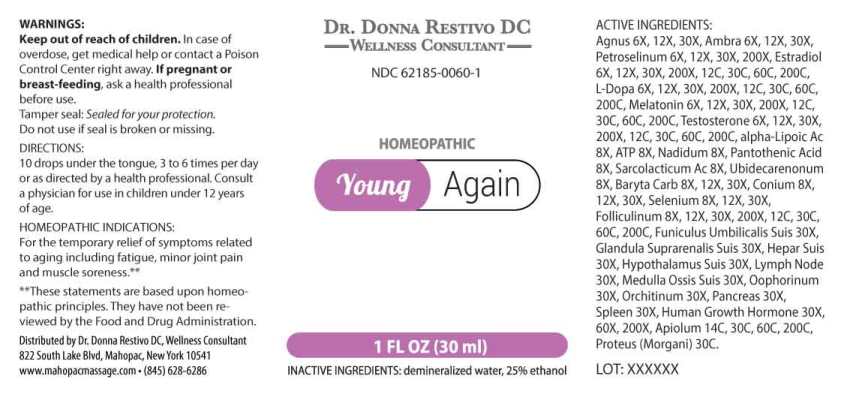 DRUG LABEL: Young Again
NDC: 62185-0060 | Form: LIQUID
Manufacturer: Dr. Donna Restivo DC
Category: homeopathic | Type: HUMAN OTC DRUG LABEL
Date: 20230110
DEA Schedule: CIII

ACTIVE INGREDIENTS: CHASTE TREE FRUIT 6 [hp_X]/1 mL; AMBERGRIS 6 [hp_X]/1 mL; PETROSELINUM CRISPUM WHOLE 6 [hp_X]/1 mL; ESTRADIOL 6 [hp_X]/1 mL; LEVODOPA 6 [hp_X]/1 mL; MELATONIN 6 [hp_X]/1 mL; TESTOSTERONE 6 [hp_X]/1 mL; ADENOSINE TRIPHOSPHATE DISODIUM 8 [hp_X]/1 mL; .ALPHA.-LIPOIC ACID 8 [hp_X]/1 mL; NADIDE 8 [hp_X]/1 mL; PANTOTHENIC ACID 8 [hp_X]/1 mL; LACTIC ACID, L- 8 [hp_X]/1 mL; UBIDECARENONE 8 [hp_X]/1 mL; BARIUM CARBONATE 8 [hp_X]/1 mL; CONIUM MACULATUM FLOWERING TOP 8 [hp_X]/1 mL; SELENIUM 8 [hp_X]/1 mL; ESTRONE 8 [hp_X]/1 mL; SUS SCROFA UMBILICAL CORD 30 [hp_X]/1 mL; SUS SCROFA ADRENAL GLAND 30 [hp_X]/1 mL; PORK LIVER 30 [hp_X]/1 mL; BOS TAURUS HYPOTHALAMUS 30 [hp_X]/1 mL; SUS SCROFA LYMPH 30 [hp_X]/1 mL; SUS SCROFA BONE MARROW 30 [hp_X]/1 mL; SUS SCROFA OVARY 30 [hp_X]/1 mL; SUS SCROFA TESTICLE 30 [hp_X]/1 mL; SUS SCROFA PANCREAS 30 [hp_X]/1 mL; SUS SCROFA SPLEEN 30 [hp_X]/1 mL; SOMATROPIN 30 [hp_X]/1 mL; APIOLE (PARSLEY) 14 [hp_C]/1 mL; PROTEUS MORGANII 30 [hp_C]/1 mL
INACTIVE INGREDIENTS: WATER; ALCOHOL

DRUG FACTS:

ACTIVE INGREDIENTS:

Agnus Castus 6X, 12X, 30X, Ambra Grisea 6X, 12X, 30X, Petroselinum Sativum 6X, 12X, 30X, 200X, Estradiol 6X, 12X, 30X, 200X, 12C, 30C, 60C, 200C, L-Dopa 6X, 12X, 30X, 200X, 12C, 30C, 60C, 200C, Melatonin 6X, 12X, 30X, 200X, 12C, 30C, 60C, 200C, Testosterone 6X, 12X, 30X, 200X, 12C, 30C, 60C, 200C, Adenosinum Triphosphoricum Dinatrum 8X, Alpha-Lipoicum Acidum 8X, Nadidum 8X, Pantothenic Acid 8X, Sarcolacticum Acidum 8X, Ubidecarenonum 8X, Baryta Carbonica 8X, 12X, 30X, Conium Maculatum 6X, 12X, 30X, Selenium Metallicum 8X, 12X, 30X, Folliculinum 8X, 12X, 30X, 200X, 12C, 30C, 60C, 200C, Funiculus Umbilicalis Suis 30X, Glandula Suprarenalis Suis 30X, Hepar Suis 30X, Hypothalamus Suis 30X, Lymph Node (Suis) 30X, Medulla Ossis Suis 30X, Oophorinum (Suis) 30X, Orchitinum (Suis) 30X, Pancreas Suis 30X, Spleen (Suis) 30X, Human Growth Hormone 30X, 60X, 200X, Apiolum 14C, 30C, 60C, 200C, Proteus (Morgani) 30C.

HOMEOPATHIC INDICATIONS:

For temporary relief of symptoms related to aging including fatigue, minor joint pain and muscle soreness.**

**These statements are based upon homeopathic principles. They have not been reviewed by the Food and Drug Administration.

WARNINGS:

Keep out of reach of children. In case of overdose, get medical help or contact or a Poison Control Center right away.

If pregnant or breast-feeding, ask a health professional before use.

Tamper seal: "Sealed for Your Protection." Do not use if seal is broken or missing.

Keep out of reach of children. In case of overdose, get medical help or contact or a Poison Control Center right away.

DIRECTIONS:

10 drops under the tongue, 3 to 6 times per day or as directed by a health professional. Consult a physician for use in children under 12 years of age.

HOMEOPATHIC INDICATIONS:

For temporary relief of symptoms related to aging including fatigue, minor joint pain and muscle soreness.**

**These statements are based upon homeopathic principles. They have not been reviewed by the Food and Drug Administration.

INACTIVE INGREDIENTS:

demineralized water, 25% ethanol

QUESTIONS:

Distributed by Dr. Donna Restivo DC, Wellness Consultant
822 South Lake Blvd, Mahopac, New York 10541
www.mahopacmassage.com • (845) 628-6286

PACKAGE LABEL DISPLAY:

DR. DONNA RESTIVO DC
WELLNESS CONSULTANT
NDC 62185-0060-1
HOMEOPATHIC

Young Again

1 FL OZ (30 ml)